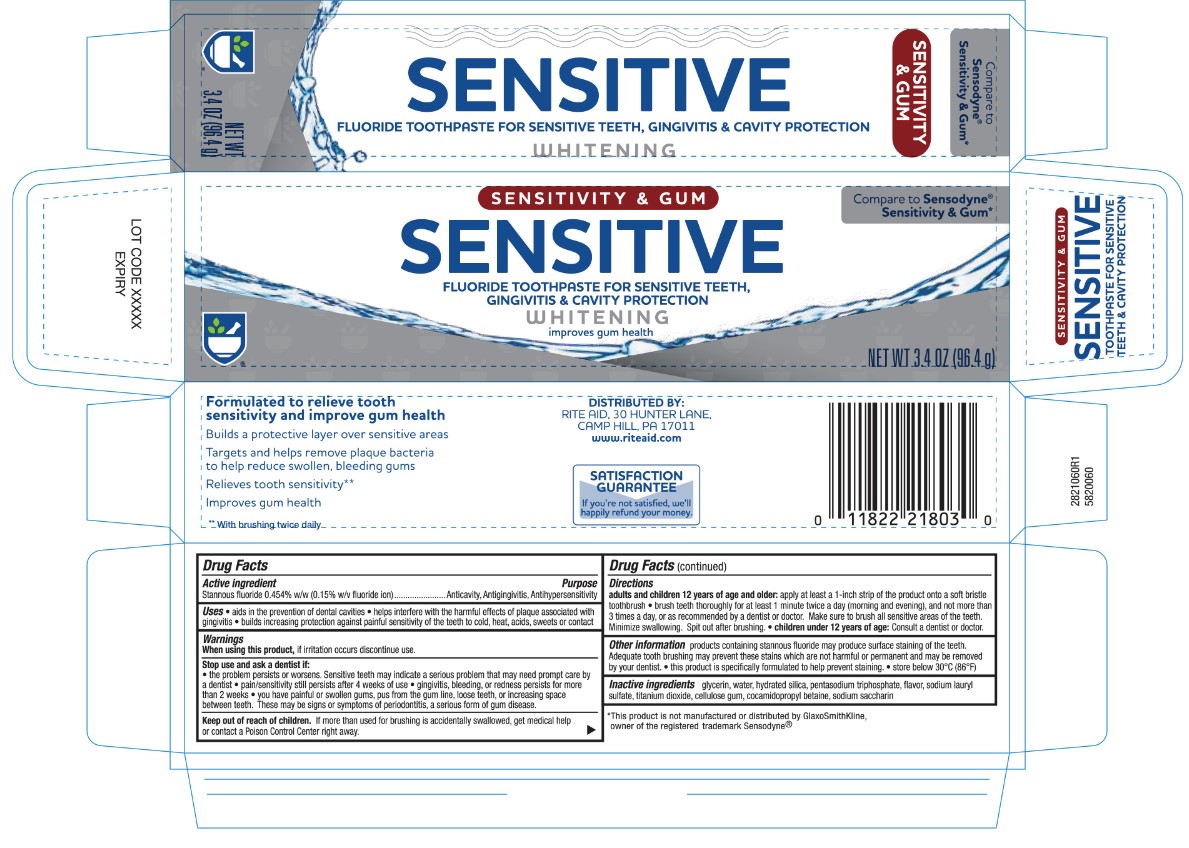 DRUG LABEL: Rite Aid Sensitivity and Gum
NDC: 11822-5060 | Form: PASTE, DENTIFRICE
Manufacturer: Rite Aid
Category: otc | Type: HUMAN OTC DRUG LABEL
Date: 20251113

ACTIVE INGREDIENTS: STANNOUS FLUORIDE 0.15 g/100 g
INACTIVE INGREDIENTS: SODIUM TRIPOLYPHOSPHATE ANHYDROUS; COCAMIDOPROPYL BETAINE; WATER; SACCHARIN SODIUM; CARBOXYMETHYLCELLULOSE SODIUM; HYDRATED SILICA; TITANIUM DIOXIDE; SODIUM LAURYL SULFATE; GLYCERIN

5820060 Rite Aid Sensitivity and Gum (8015053)

ACTIVE INGREDIENT

Stannous Fluoride 0.454% w/w (0.15% w/v fluoride ion) ...... Acticavity, Antigingivitis, Anithypersensitivity

DOSAGE AND ADMINISTRATION

Aids in the prevention of dental cavities. Helps interfere with the harmful effects of plaque associated with gingivitis. Builds increasing protection against painful sensitivity of the teeth to cold, heat, acids, sweets, or contact.

INDICATIONS AND USAGE

Adults and children 12 years of age and older: apply at least a 1-inch strip of the product onto a soft bristle toothbrush. Brush teeth thoroughly for at least 1 minute twice a day (morning and evening), and not more than 3 times a day, or as recommended by a dentist or doctor. Make sure to brush all sensitive areas of the teeth. Minimize swallowing. Spit out after brushing. Children under 12 years of age: consult a dentist or doctor.

Keep out of reach of children. If more than used for brushing is accidentally swallowed, get medical help or contact a poision control center right away.

PURPOSE

Products containing stannous fluoride may produce surface staining of the teeth. Adquate tooth brushing may prevent these stains which are not harmful or permanent and may be removed by your dentist. This product is specifically formulated to prevent staining. Store below 30C or 86F.

When using this product, if irritation occurs discontinue use. Stop use and ask a dentist if the problem persists or worsens. Sensitive teeth may indicate a serious problem that may need prompt care by a dentist. Pain/sensitivity still persists after 4 weeks of use. Gingivitis, bleeding, or redness persists for more than 2 weeks. You have painful or swollen gums, pus from the gum line, loose teeth, or increasing space between teeth. These may be signs or symptoms of periodontitis, a serious form of gum disease.

INACTIVE INGREDIENT

glycerin, water, hydrated silica, petasodium tryiphosphate, flavor, sodium lauryl sulfate, titanium dioxide, cellulose gum, cocamiodpropyl betaine, sodium saccharin.